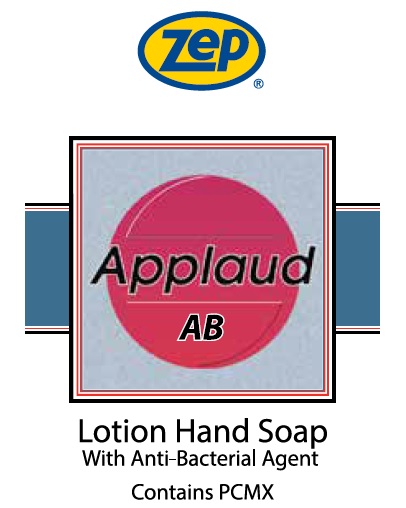 DRUG LABEL: Zep Applaud AB
NDC: 66949-123 | Form: LIQUID
Manufacturer: Zep Inc.
Category: otc | Type: HUMAN OTC DRUG LABEL
Date: 20251226

ACTIVE INGREDIENTS: CHLOROXYLENOL 0.3 g/100 mL
INACTIVE INGREDIENTS: LAURIC ACID; POTASSIUM OLEATE; D&C RED NO. 33; EDETATE SODIUM; WATER; BUTYLATED HYDROXYTOLUENE; COCO DIISOPROPANOLAMIDE; SODIUM CHLORIDE; METHACRYLATE/METHOXY PEG-10 MALEATE/STYRENE COPOLYMER; ISOPROPYL ALCOHOL; FD&C RED NO. 4

66949-123 / 3385 Applaud AB

Active Ingredient

Chloroxylenol 0.3%

Purpose

Antiseptic

Uses

Hand washing to decrease bacteria on skin.

Warnings

- For external use only.

Do not use in the eyes; if in eyes, rinse promptly and thoroughly with water.

When using this product

- Do not swallow.
- If swallowed, do not induce vomiting and if individual is conscious, give large quantities of water to drink and consult a physician immediately.

Stop use ask a doctor if skin irritation or redness persists for more than 72 hours.

Keep out of reach of children except under adult supervision.

Directions

- Wet hands with water.
- Place hands under dispenser.
- Apply liquid soap.
- Massage soap into hands and wrists, emphasizing back of hands, knuckles, and cuticles.
- Rinse thoroughly.

Other information

- Store at room temperature.
- Do not freeze.
- Dispose in accordance with all applicable federal, state and local regulations.

Inactive ingredients

Water, Potassium Oleate , Cocamide DIPA, Lauric Acid, Sodium Chloride, Tetrasodium EDTA, Acrylates/PEG-10 maleate/Styrene Copolymer, Isopropyl Alcohol, Fragrance, BHT, Red 4, Red 33

Questions or comments?

Call 1-877-BUY-ZEP (1-877-428-9937)